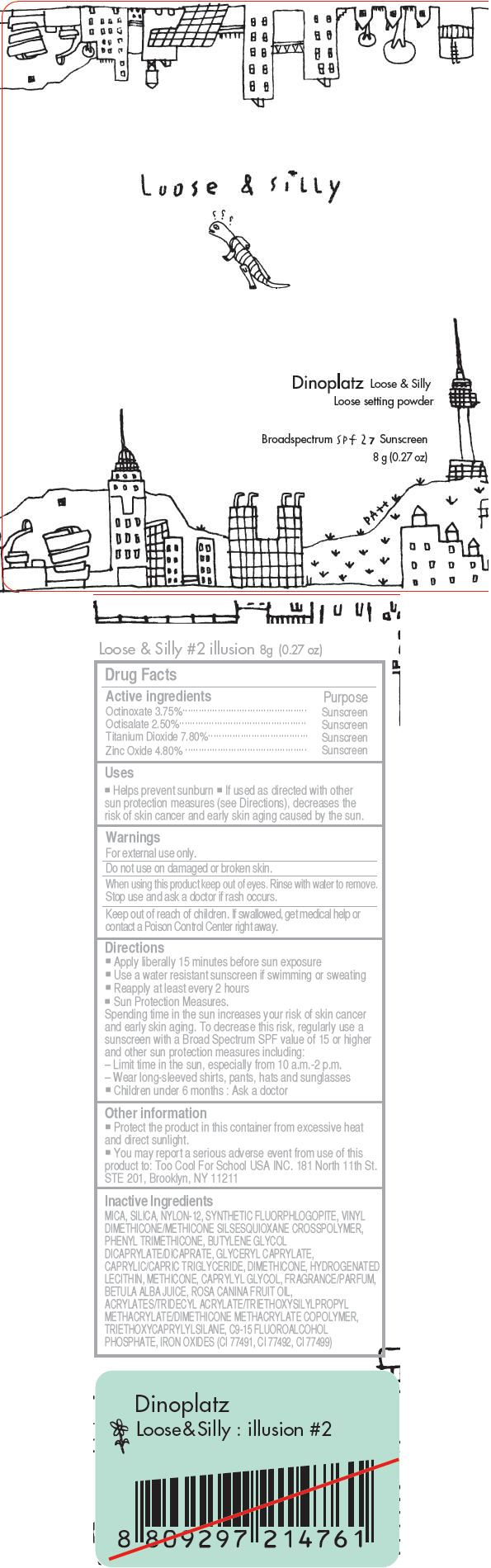 DRUG LABEL: Too Cool For School 
NDC: 69926-005 | Form: POWDER
Manufacturer: Too Cool For School USA, Inc
Category: otc | Type: HUMAN OTC DRUG LABEL
Date: 20150624

ACTIVE INGREDIENTS: Octinoxate 3.75 g/100 g; Octisalate 2.5 g/100 g; Titanium Dioxide 7.8 g/100 g; Zinc Oxide 4.8 g/100 g
INACTIVE INGREDIENTS: MICA; SILICON DIOXIDE; NYLON-12; PHENYL TRIMETHICONE; BUTYLENE GLYCOL DICAPRYLATE/DICAPRATE; GLYCERYL CAPRYLATE; MEDIUM-CHAIN TRIGLYCERIDES; DIMETHICONE; HYDROGENATED SOYBEAN LECITHIN; CAPRYLYL GLYCOL; BETULA PUBESCENS RESIN; ROSA CANINA FRUIT OIL; TRIETHOXYCAPRYLYLSILANE; FERRIC OXIDE RED

Too Cool For School
DINOPLATZ LOOSE & SILLY #2 Illusion

Drug Facts

ACTIVE INGREDIENT

Active ingredients | Purpose
Octinoxate 3.75% | Sunscreen
Octisalate 2.50% | Sunscreen
Titanium Dioxide 7.80% | Sunscreen
Zinc Oxide 4.80% | Sunscreen

Uses

- Helps prevent sunburn
- If used as directed with other sun protection measures (see Directions), decreases the risk of skin cancer and early skin aging caused by the sun.

Warnings

For external use only.

Do not use on damaged or broken skin.

When using this product keep out of eyes. Rinse with water to remove.

Stop use and ask a doctor if rash occurs.

Keep out of reach of children. If swallowed, get medical help or contact a Poison Control Center right away.

Directions

- Apply liberally 15 minutes before sun exposure
- Use a water resistant sunscreen if swimming or sweating
- Reapply at least every 2 hours
- Sun Protection Measures.
  Spending time in the sun increases your risk of skin cancer and early skin aging. To decrease this risk, regularly use a sunscreen with a Broad Spectrum SPF value of 15 or higher and other sun protection measures including:
  – Limit time in the sun, especially from 10 a.m.-2 p.m.
  – Wear long-sleeved shirts, pants, hats and sunglasses
- Children under 6 months : Ask a doctor

Other information

- Protect the product in this container from excessive heat and direct sunlight.
- You may report a serious adverse event from use of this product to: Too Cool For School USA INC. 181 North 11th St. STE 201, Brooklyn, NY 11211

Inactive Ingredients

MICA, SILICA, NYLON-12, SYNTHETIC FLUORPHLOGOPITE, VINYL DIMETHICONE/METHICONE SILSESQUIOXANE CROSSPOLYMER, PHENYL TRIMETHICONE, BUTYLENE GLYCOL DICAPRYLATE/DICAPRATE, GLYCERYL CAPRYLATE, CAPRYLIC/CAPRIC TRIGLYCERIDE, DIMETHICONE, HYDROGENATED LECITHIN, METHICONE, CAPRYLYL GLYCOL, FRAGRANCE/PARFUM, BETULA ALBA JUICE, ROSA CANINA FRUIT OIL, ACRYLATES/TRIDECYL ACRYLATE/TRIETHOXYSILYLPROPYL METHACRYLATE/DIMETHICONE METHACRYLATE COPOLYMER, TRIETHOXYCAPRYLYLSILANE, C9-15 FLUOROALCOHOL PHOSPHATE, IRON OXIDES (CI 77491, CI 77492, CI 77499)

Dist. by©Too Cool For Shhol USA Inc. Brooklyn, NY 11211

PRINCIPAL DISPLAY PANEL - 8 g Bottle Carton

Loose & Silly

Dinoplatz Loose & Silly
Loose setting powder

Broadspectrum spf 27 Sunscreen

8g (0.27oz)